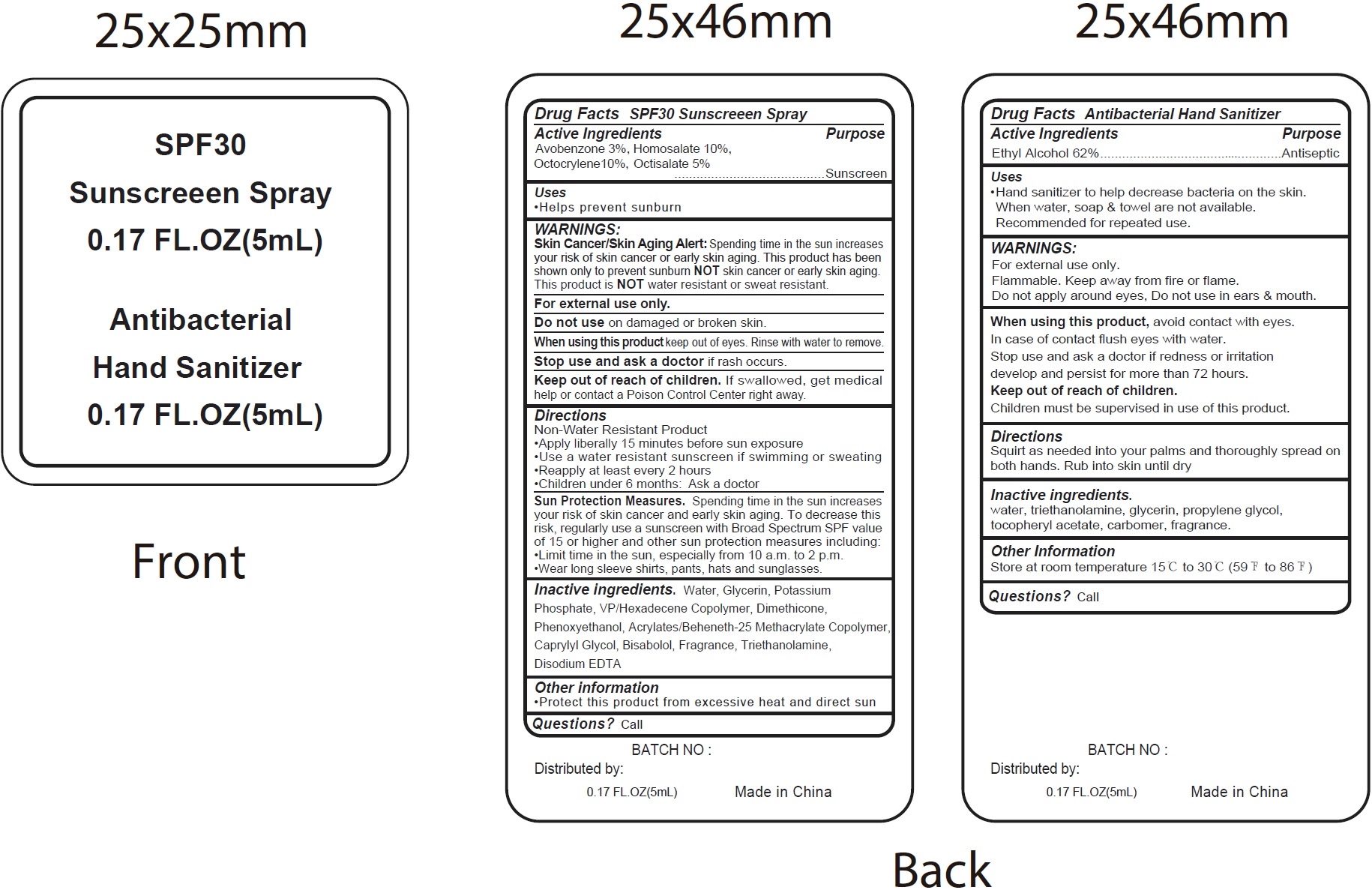 DRUG LABEL: SPF30 Sunscreen and Antibacterial Hand Sanitizer
NDC: 70412-817 | Form: KIT | Route: TOPICAL
Manufacturer: Zhejiang Ayan Biotech Co., Ltd.
Category: otc | Type: HUMAN OTC DRUG LABEL
Date: 20231106

ACTIVE INGREDIENTS: ALCOHOL 620 mg/1 mL; AVOBENZONE 30 mg/1 mL; HOMOSALATE 100 mg/1 mL; OCTOCRYLENE 100 mg/1 mL; OCTISALATE 50 mg/1 mL
INACTIVE INGREDIENTS: WATER; TROLAMINE; GLYCERIN; PROPYLENE GLYCOL; CARBOXYPOLYMETHYLENE; WATER; GLYCERIN; POTASSIUM PHOSPHATE, UNSPECIFIED FORM; VINYLPYRROLIDONE/HEXADECENE COPOLYMER; DIMETHICONE; PHENOXYETHANOL; CAPRYLYL GLYCOL; LEVOMENOL; TROLAMINE; EDETATE DISODIUM ANHYDROUS

SPF30 Sunscreen Spray, & Antibacterial Hand Sanitizer

Active Ingredients

Ethyl Alcohol 62%

Purpose

Antiseptic

Uses

•Hand sanitizer to help decrease bacteria on the skin. When water, soap & towel are not available. Recommended for repeated use.

WARNINGS:

For external use only. Flammable. Keep away from fire or flame.

Do not apply around eyes,

Do not use

in ears & mouth.

When using this product

avoid contact with eyes. In case of contact flush eyes with water.

Stop use and ask a doctor

if redness or irritation develop and persist for more than 72 hours.

Keep out of reach of children.

Children must be supervised in use of this product.

Directions

Squirt as needed into your palms and thoroughly spread on both hands. Rub into skin until dry

Inactive ingredients.

water, triethanolamine, glycerin, propylene glycol, tocopheryl acetate, carbomer, fragrance.

Other Information

Store at room temperature 15°C to 30°C (59° F to 86° F)

Questions?

Call

Active Ingredients

Avobenzone 3%, Homosalate 10%,

Octocrylene10%, Octisalate 5%

Purpose

Sunscreen

Uses

• Helps prevent sunburn

WARNINGS:

Spending time in the sun increases your risk of skin cancer or early skin aging. This product has been shown only to prevent sunburn skin cancer or early skin aging. This product is water resistant or sweat resistant. Skin Cancer/Skin Aging Alert: NOTNOT

For external use only.

Do not use

on damaged or broken skin.

When using this product

keep out of eyes. Rinse with water to remove.

Stop use and ask a doctor

if rash occurs.

Keep out of reach of children.

If swallowed, get medical help or contact a Poison Control Center right away.

Directions

Non-Water Resistant Product • Apply liberally 15 minutes before sun exposure • Use a water resistant sunscreen if swimming or sweating • Reapply at least every 2 hours • Children under 6 months: Ask a doctor

Spending time in the sun increases your risk of skin cancer and early skin aging. To decrease this risk, regularly use a sunscreen with Broad Spectrum SPF value of 15 or higher and other sun protection measures including: •Limit time in the sun, especially from 10 a.m. to 2 p.m. •Wear long sleeve shirts, pants, hats and sunglasses. Sun Protection Measures.

Inactive ingredients.

Water, Glycerin, Potassium Phosphate, VP/Hexadecene Copolymer, Dimethicone, Phenoxyethanol, Acrylates/Beheneth-25 Methacrylate Copolymer, Caprylyl Glycol, Bisabolol, Fragrance, Triethanolamine, Disodium EDTA

Other information

•Protect this product from excessive heat and direct sun

Questions?

Call